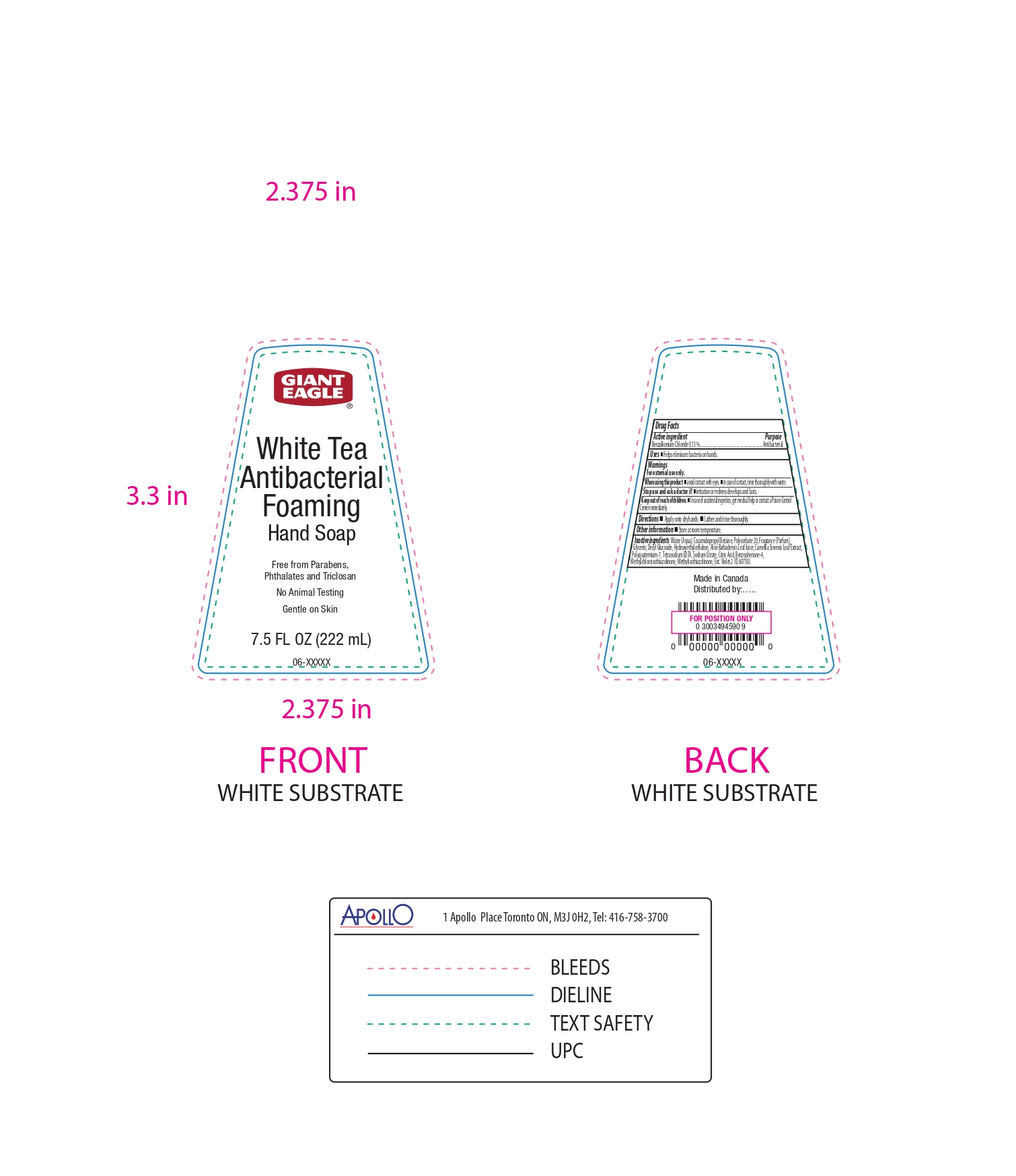 DRUG LABEL: Giant Eagle
NDC: 56194-502 | Form: SOAP
Manufacturer: GIANT EAGLE
Category: otc | Type: HUMAN OTC DRUG LABEL
Date: 20250206

ACTIVE INGREDIENTS: BENZALKONIUM CHLORIDE 130 mg/100 mL
INACTIVE INGREDIENTS: COCAMIDOPROPYL BETAINE; POLYSORBATE 20; DECYL GLUCOSIDE; EXT. VIOLET 2; POLYQUATERNIUM-7; BENZOPHENONE-4; ALOE VERA LEAF; HYDROXYETHYL CELLULOSE, UNSPECIFIED; SODIUM CITRATE; METHYLCHLOROISOTHIAZOLINONE; WATER; TETRASODIUM EDTA; GLYCERIN; CITRIC ACID; METHYLISOTHIAZOLINONE; FRAGRANCE CLEAN ORC0600327; CAMELLIA SINENSIS LEAF

56194-502-01, White Tea Antibacterial Liq Hand Soap

Active Ingredient.

Benzalkonium Chloride (0.13%)

Purpose

Antibacterial

Uses

Helps eliminate bacteria on hands.

Warnings

For external use only

When using this product

Avoid contact with eyes. In case of contact, rinse thoroughly with water.

Stop use and ask a doctor if

irritation or redness develops and lasts

Keep out of reach of children.

In case of accidental ingestion, get medical help or contact a Poison Control Center immediately.

Directions

- Apply onto wet hands
- Lather and rinse thoroughly.

Other Information

Store at room temperature

Inactive Ingredients

Water (Aqua), Cocamidopropyl Betaine, Polysorbate 20, Fragrance (Parfum), Glycerin, Decyl Glucoside, Hydroxyethylcellulose, Aloe Barbadensis Leaf Juice, Camellia Sinensis Leaf Extract, Polyquaternium-7, Tetrasodium EDTA, Sodium Citrate, Citric Acid, Benzophenone-4, Methylchloroisothiazolinone, Methylisothiazolinone, Ext. Violet 2 (CI 60730).